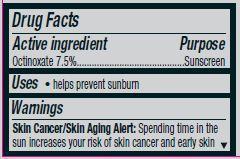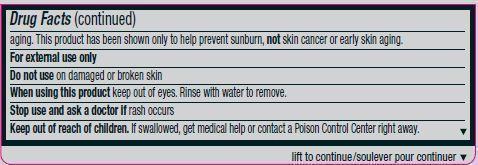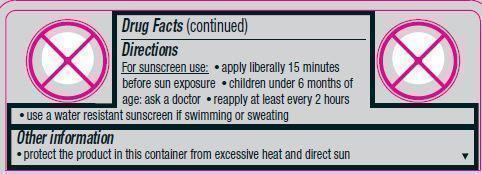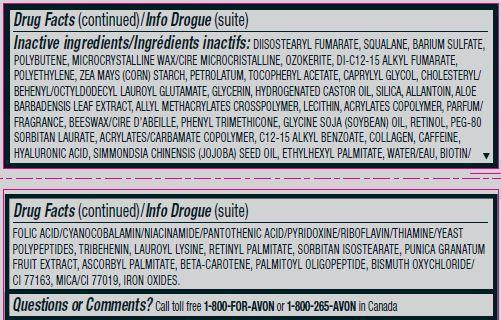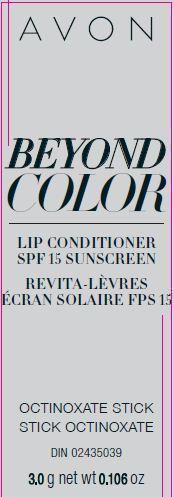 DRUG LABEL: Beyond Color
NDC: 10096-0328 | Form: LIPSTICK
Manufacturer: New Avon LLC
Category: otc | Type: HUMAN OTC DRUG LABEL
Date: 20190101

ACTIVE INGREDIENTS: OCTINOXATE 75 mg/1 g
INACTIVE INGREDIENTS: WATER

Beyond Color Lip Conditioner SPF 15

Active ingredient
Octinoxate 7.5%................................

Purpose
...............................Sunscreen

Uses
• helps prevent sunburn

Warnings
Skin Cancer/Skin Aging Alert: Spending time in the sun increases your risk of skin cancer and early skin aging. This product has been shown only to help prevent sunburn, not skin cancer or early skin aging.
For external use only

Do not use on damaged or broken skin

When using this product keep out of eyes. Rinse with water to remove.

Stop use and ask a doctor if rash occurs

Keep out of reach of children. If swallowed, get medical help or contact a poison control center right away.

Directions

For sunscreen use:
• apply liberally 15 minutes before sun exposure
• children under 6 months of age: ask a doctor
• reapply at least every 2 hours
• use a water resistant sunscreen if swimming or sweating

Other information
• protect the product in this container from excessive heat and direct sun

INACTIVE INGREDIENT

Inactive ingredients: DIISOSTEARYL FUMARATE, SQUALANE, BARIUM SULFATE, POLYBUTENE, MICROCRYSTALLINE WAX/CIRE MICROCRISTALLINE, OZOKERITE, DI-C12-15 ALKYL FUMARATE, POLYETHYLENE, ZEA MAYS (CORN) STARCH, PETROLATUM, TOCOPHERYL ACETATE, CAPRYLYL GLYCOL, CHOLESTERYL/BEHENYL/OCTYLDODECYL LAUROYL GLUTAMATE, GLYCERIN, HYDROGENATED CASTOR OIL, SILICA, ALLANTOIN, ALOE BARBADENSIS LEAF EXTRACT, ALLYL METHACRYLATES CROSSPOLYMER, LECITHIN, ACRYLATES COPOLYMER, PARFUM/FRAGRANCE, BEESWAX/CIRE D’ABEILLE, PHENYL TRIMETHICONE, GLYCINE SOJA (SOYBEAN) OIL, RETINOL, PEG-80SORBITAN LAURATE, ACRYLATES/CARBAMATE COPOLYMER, C12-15 ALKYL BENZOATE, COLLAGEN, CAFFEINE,HYALURONIC ACID, SIMMONDSIA CHINENSIS (JOJOBA) SEED OIL, ETHYLHEXYL PALMITATE, WATER/EAU, BIOTIN/FOLIC ACID/CYANOCOBALAMIN/NIACINAMIDE/PANTOTHENIC ACID/PYRIDOXINE/RIBOFLAVIN/THIAMINE/YEAST POLYPEPTIDES, TRIBEHENIN, LAUROYL LYSINE, RETINYL PALMITATE, SORBITAN ISOSTEARATE, PUNICA GRANATUMFRUIT EXTRACT, ASCORBYL PALMITATE, BETA-CAROTENE, PALMITOYL OLIGOPEPTIDE, BISMUTH OXYCHLORIDE/CI 77163, MICA/CI 77019, IRON OXIDES.

Questions or Comments?
Call toll free 1-800-FOR-AVON or 1-800-265-AVON in Canada